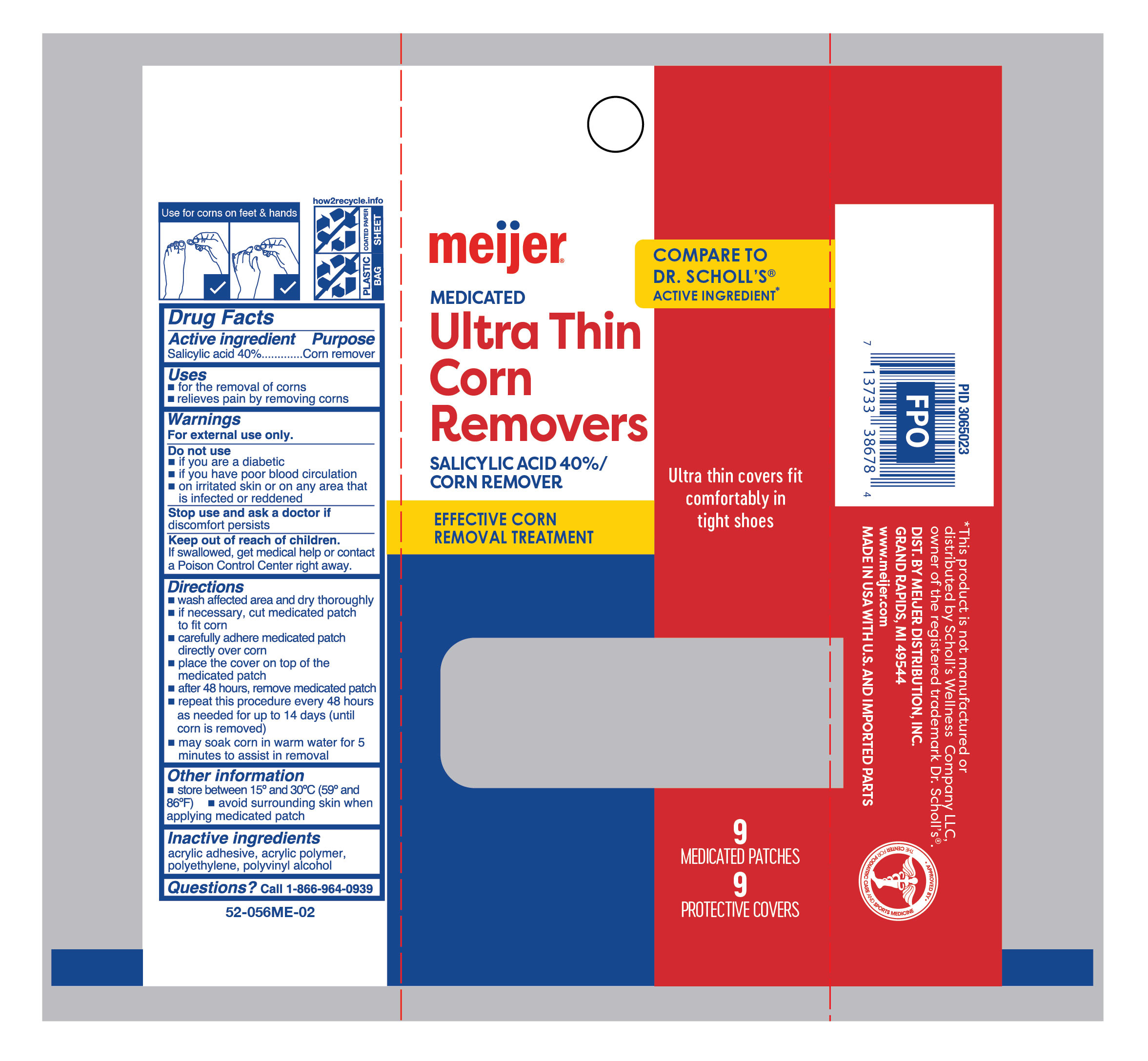 DRUG LABEL: Medicated Corn Removers
NDC: 79481-1613 | Form: PATCH
Manufacturer: Meijer Distribution Inc
Category: otc | Type: HUMAN OTC DRUG LABEL
Date: 20260115

ACTIVE INGREDIENTS: SALICYLIC ACID 400 mg/1 g
INACTIVE INGREDIENTS: POLYVINYL ALCOHOL, UNSPECIFIED; HIGH DENSITY POLYETHYLENE

Meijer Ultra Thin Corn Removers

Active ingredient

Salicylic acid 40%

Purpose

Corn remover

Use

- for the removal of corns
- relieves pain by removing corns

Warnings

For external use only.

Do not use

- if you are a diabetic
- if you have poor blood circulation
- on irritated skin, on any area that is infected or reddened

Keep out of reach of children.

If swallowed, get medical help or contact a Poison Control Center right away.

Stop use and ask a doctor if

if discomfort persists

Directions

- wash affected area and dry area thoroughly
- if necessary, cut medicated patch to fit corn
- apply adhesive side of medicated patch onto corn
- place the cover on top of the medicated patch
- after 48 hours, remove medicated patch
- repeat procedure every 48 hours as needed for up to 14 days (until corn is removed)
- may soak corn in warm water for 5 minutes to assist in removal

Other information

- store between 15°C to 30°C (59°F to 86°F)
- avoid surrounding skin when applying medicated patch

Inactive ingredients

acrylic adhesive, acrylic polymer, polyethylene, polyvinyl alcohol

Questions?

1-866-964-0939

Principal Display Panel

meijer

MEDICATED

Ultra Thin

Corn Remover

Salicylic Acid 40%/Corn Remover

Effective corn removal treatment

Ultra thin covers fit comfortably in tight shoes

9 Medicated Patches

9 Protective Covers